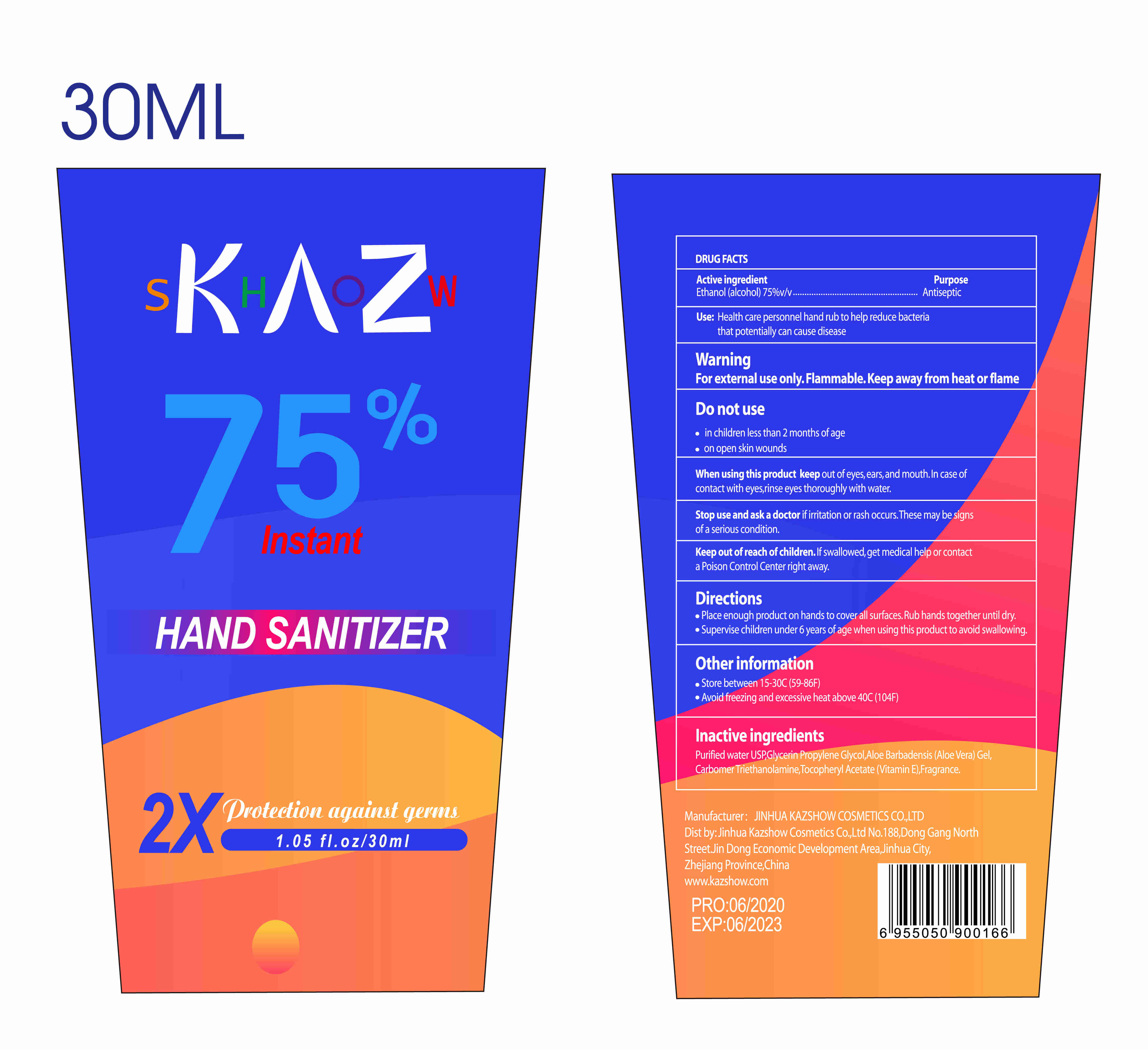 DRUG LABEL: KAZSHOW HAND SANITIZER
NDC: 54248-008 | Form: GEL
Manufacturer: Jinhua Kazixiu Cosmetic Co.,Ltd.
Category: otc | Type: HUMAN OTC DRUG LABEL
Date: 20200713

ACTIVE INGREDIENTS: ALCOHOL 22.5 mL/30 mL
INACTIVE INGREDIENTS: WATER; TROLAMINE; .ALPHA.-TOCOPHEROL ACETATE; FRAGRANCE LAVENDER & CHIA F-153480; GLYCERIN; PROPYLENE GLYCOL; ALOE; CARBOMER HOMOPOLYMER, UNSPECIFIED TYPE

DOSAGE AND ADMINISTRATION

Store between 15-30℃

INACTIVE INGREDIENT

Purified water USP, Glycerin, Propylene Glycol,Aloe Barbadensis (Aloe Vera) Gel, Carbomer, Triethanolamine, Tocopheryl Acetate (Vitamin E), Fragrance

INDICATIONS AND USAGE

1.Place enough product onhands to cover all surfaces Rub hands together until dry.
2.Supervise children under 6 years of age when using this productto avoid swallowing.

ACTIVE INGREDIENT

Alcohol

keep out of reach of children

PURPOSE

Disinfection
Sterilization
No Rinseing

WARNINGS

1.In childrenless than2 months of age

2.on open skin wounds

3.When using this product keep out of eyesears,and mouth.In case of contact with eyes,pinse eyes thoroughly with water.

4.Stop use and ask a doctor i itation or rash occurs.These may be signs of a seious condition.
5.Keep out of reach of children.f sallwed.get medicalhelp or contact a Poison Control Center right away.